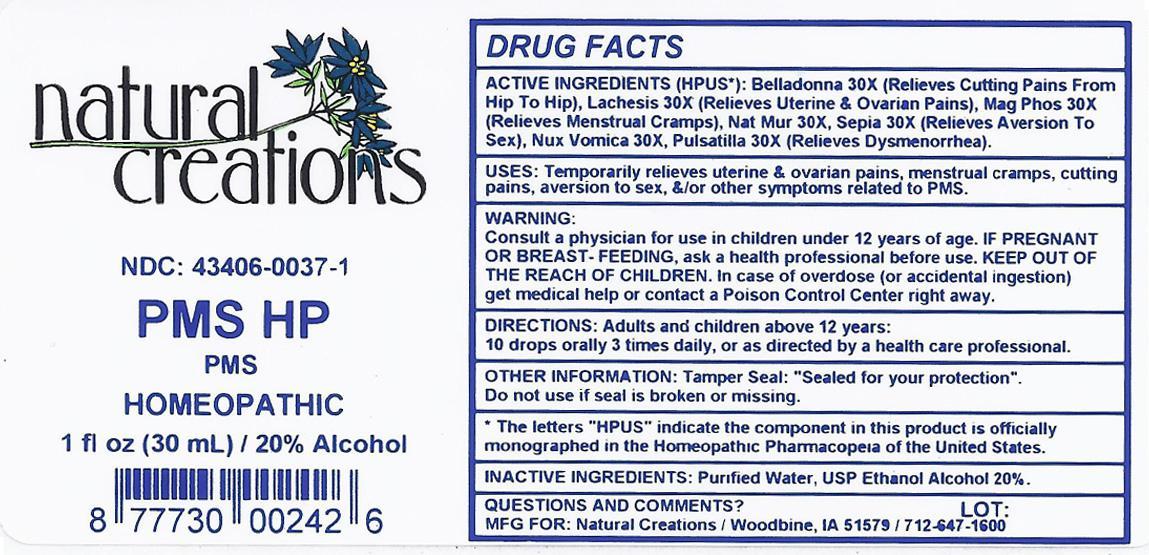 DRUG LABEL: PMS HP
NDC: 43406-0037 | Form: LIQUID
Manufacturer: Natural Creations, Inc.
Category: homeopathic | Type: HUMAN OTC DRUG LABEL
Date: 20121112

ACTIVE INGREDIENTS: ATROPA BELLADONNA 30 [hp_X]/1 mL; LACHESIS MUTA VENOM 30 [hp_X]/1 mL; MAGNESIUM PHOSPHATE, DIBASIC TRIHYDRATE 30 [hp_X]/1 mL; SODIUM CHLORIDE 30 [hp_X]/1 mL; STRYCHNOS NUX-VOMICA SEED 30 [hp_X]/1 mL; PULSATILLA VULGARIS 30 [hp_X]/1 mL; SEPIA OFFICINALIS JUICE 30 [hp_X]/1 mL
INACTIVE INGREDIENTS: WATER; ALCOHOL

PMS HP

ACTIVE INGREDIENT

ACTIVE INGREDIENTS (HPUS*): Belladonna 30X, Lachesis Mutus 30X, Magnesia Phosphorica 30X, Natrum Muriaticum 30X, Nux Vomica 30X, Pulsatilla 30X, Sepia 30X

INDICATIONS AND USAGE

USES: Temporarily relieves uterine & ovarian pains, menstrual cramps, cutting pains, aversion to sex, &/or other symptoms related to PMS.

WARNING:

Consult a physician for use in children under 12 years of age. IF PREGNANT OR BREAST-FEEDING, ask a health care professional before use. KEEP OUT OF THE REACH OF CHILDREN. In case of overdose (or accidental ingestion) get medical help or contact a Poison Control Center right away.

DOSAGE AND ADMINISTRATION

DIRECTIONS: Adults and children above 12 years: 10 drops orally 3 times daily, or as directed by a health care professional.

OTHER INFORMATION: Tamper Seal: "Sealed for your protection."

Do not use if seal is broken or missing.

REFERENCES

*The letters "HPUS" indicate the components in thye product are officially monographed in the Homeopathic Pharmacopeia of the United States.

INACTIVE INGREDIENTS: Purified Water, USP Ethanol Alcohol 20%

QUESTIONS AND COMMENTS?

MFG FOR: Natural Creations / Woodbine, IA / 51579 712.647.1600

LOT:

PURPOSE

USES: Temporarily relieves uterine & ovarian pains, menstrual cramps, cutting pains, aversion to sex, &/or other symptoms related to PMS.

KEEP OUT OF REACH OF CHILDREN

KEEP OUT OF THE REACH OF CHILDREN. In case of overdose (or accidental ingestion) get medical help or contact a Poison Control Center.

PACKAGE LABEL

NDC: 43406-0037-1

PMS HP

PMS

HOMEOPATHIC

1 fl oz (30 mL) / 20% Alcohol